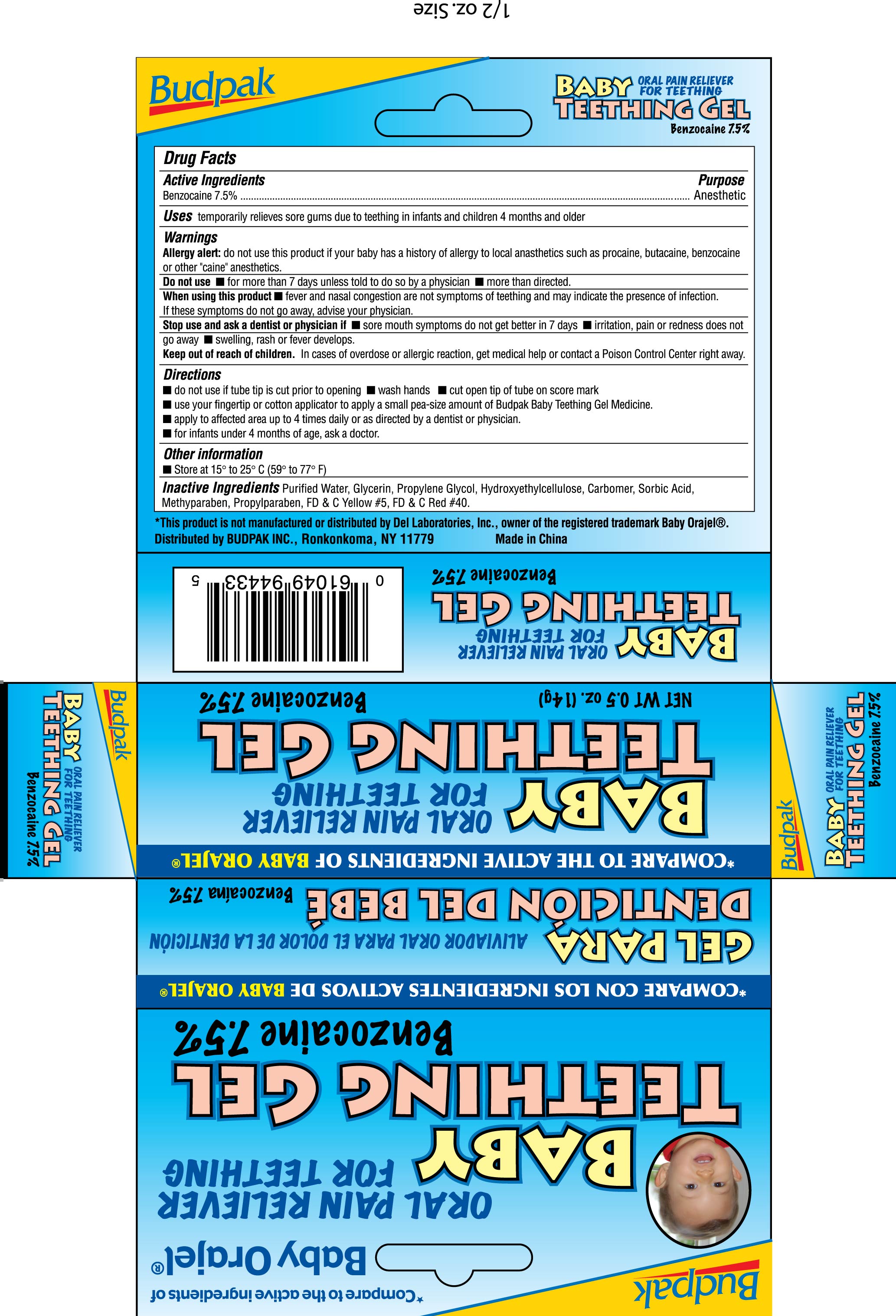 DRUG LABEL: Baby Teething Oral Pain Reliever
NDC: 27293-013 | Form: GEL
Manufacturer: Budpak Inc.
Category: otc | Type: HUMAN OTC DRUG LABEL
Date: 20100501

ACTIVE INGREDIENTS: BENZOCAINE 7.5 g/100 g
INACTIVE INGREDIENTS: WATER; GLYCERIN; PROPYLENE GLYCOL; SORBIC ACID; METHYLPARABEN; PROPYLPARABEN; FD&C YELLOW NO. 5; FD&C RED NO. 40

Drug Facts

Active Ingredient
Benzocaine 7.5%

Purpose
Anesthetic

INDICATIONS AND USAGE

Uses temporarily relieves sore gums due to teething in infants and children 4 months and older

Warnings

- Allergy alert: do not use this product if your baby has a history of allergy to local anesthetics such as procaine, butacaine or other "caine" anesthetics

Do not use

- for more than 7 days unless told to do so by a physician
- more than directed

When using this product

- fever and nasal congestion are not symptoms of teething and may indicate the presence of infection. If these symptoms do not go away, advise your physician

Stop using and ask a dentist or physician

- sore mouth symptoms do not get better in 7 days
- irritation, pain or redness does not go away
- swelling, rash or fever develops

Keep out of reach of children. In case of overdose or allergic reaction contact a Poison Control Center right away

Directions

- wash your hands
- use your fingertip or cotton applicator to apply a small pea-size amount of Budpack Baby Teething Gel Medicine.
- Apply to affected area up to 4 times daily or as directed by a dentist or physician.
- for infants under 4 months of age, ask a doctor

Other information

- Store at 15 to 25 C (59-77F)

INACTIVE INGREDIENT

Inactive Ingredients Purified water, Glycerin, Propylene Glycol, Hydroxyethylcellulose, Carbomer, Sorbic Acid, Methylparaben, Propylparaben, FDC Yellow 5, FDC Red 40

Package Label